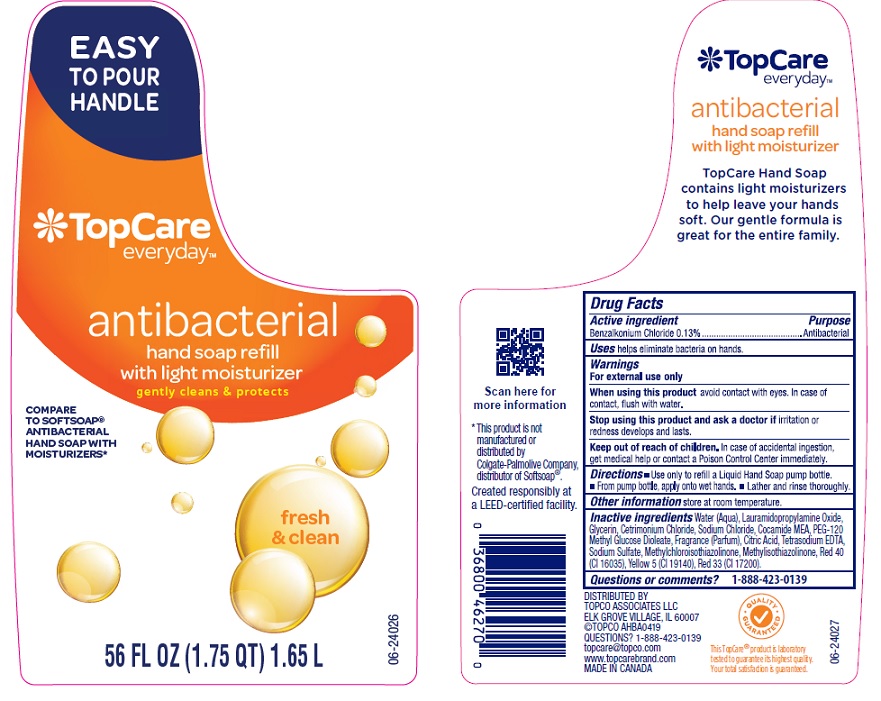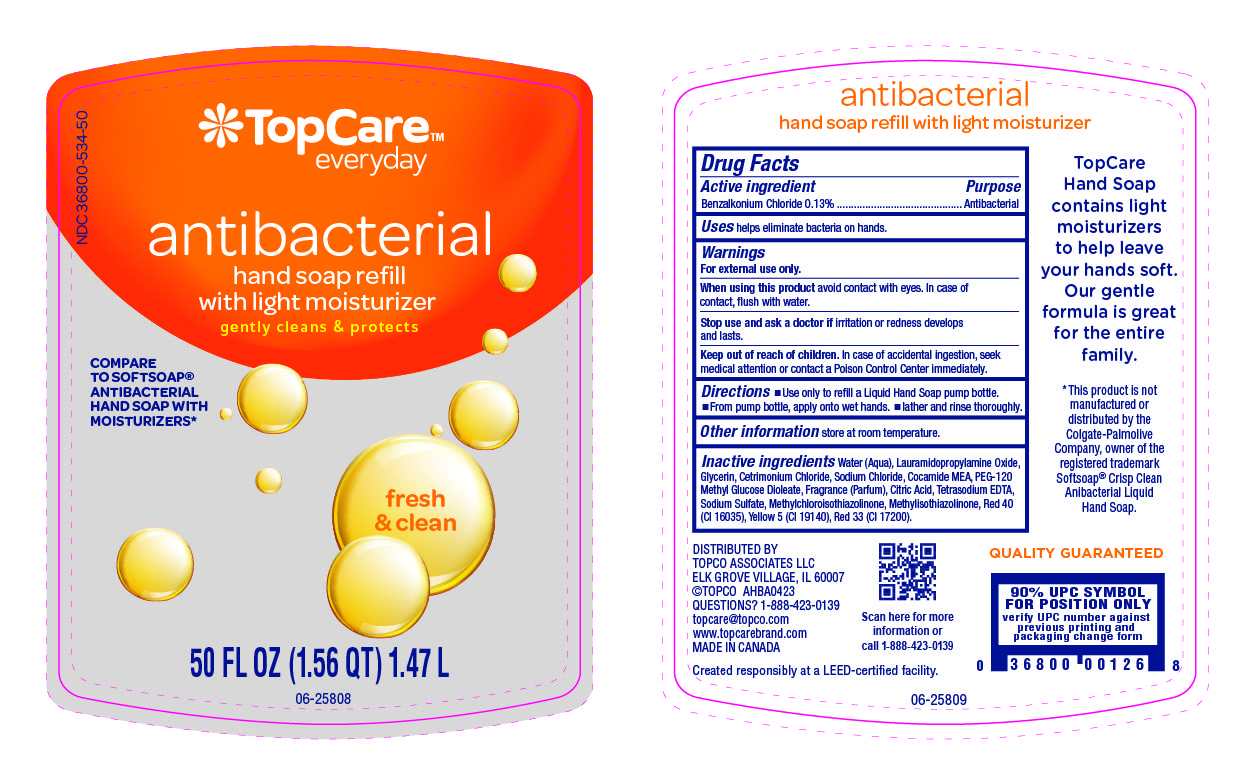 DRUG LABEL: TopCare Antibacterial Hand Fresh and Clean
NDC: 36800-534 | Form: LIQUID
Manufacturer: Topco Associates LLC
Category: otc | Type: HUMAN OTC DRUG LABEL
Date: 20240509

ACTIVE INGREDIENTS: BENZALKONIUM CHLORIDE 1.3 mg/1 mL
INACTIVE INGREDIENTS: LAURAMIDOPROPYLAMINE OXIDE; GLYCERIN; CETRIMONIUM CHLORIDE; SODIUM CHLORIDE; COCO MONOETHANOLAMIDE; PEG-120 METHYL GLUCOSE DIOLEATE; CITRIC ACID MONOHYDRATE; FRAGRANCE CLEAN ORC0600327; EDETATE SODIUM; SODIUM SULFATE; METHYLCHLOROISOTHIAZOLINONE; METHYLISOTHIAZOLINONE; FD&C RED NO. 40; FD&C YELLOW NO. 5; WATER; D&C RED NO. 33

NDC 36800-534, Topcare anti bacterial Hand soap

Active ingredient

Benzalkonium chloride 0.13%

Purpose

Antibacterial

Uses

helps eliminate bacteria on hands.

Warnings

For external use only

When using this product

avoid contact with eyes. In case of contac, flush with water.

Stop using this product and ask a doctor if

irritation or redness develops and lasts.

Keep out of reach of children.

In case of accidental ingestion, get medical help or contact a Poison Control Center immediately.

Directions

- Use only to refill a Liquid Hand Soap pump bottle.
- From pump bottle, apply onto wet hands.
- Lather and rinse thoroughly.

Other information

store at room temperature.

Inactive ingredients

Water (Aqua), Lauramidopropylamine Oxide, Glycerin, Cetrimonium Chloride, Sodium Chloride, Cocamide MEA, PEG-120 Methyl Glucose Dioleate, Fragrance (Parfum), Citric Acid, Tetrasodium EDTA, Sodium Sulfate, Methylchloroisothiazolinone, Methylisothiazolinone, Red 40 (CI 16035), Yellow 5 (CI 19140), Red 33 (CI 17200).

Questions or comments?

1-888-423-0139